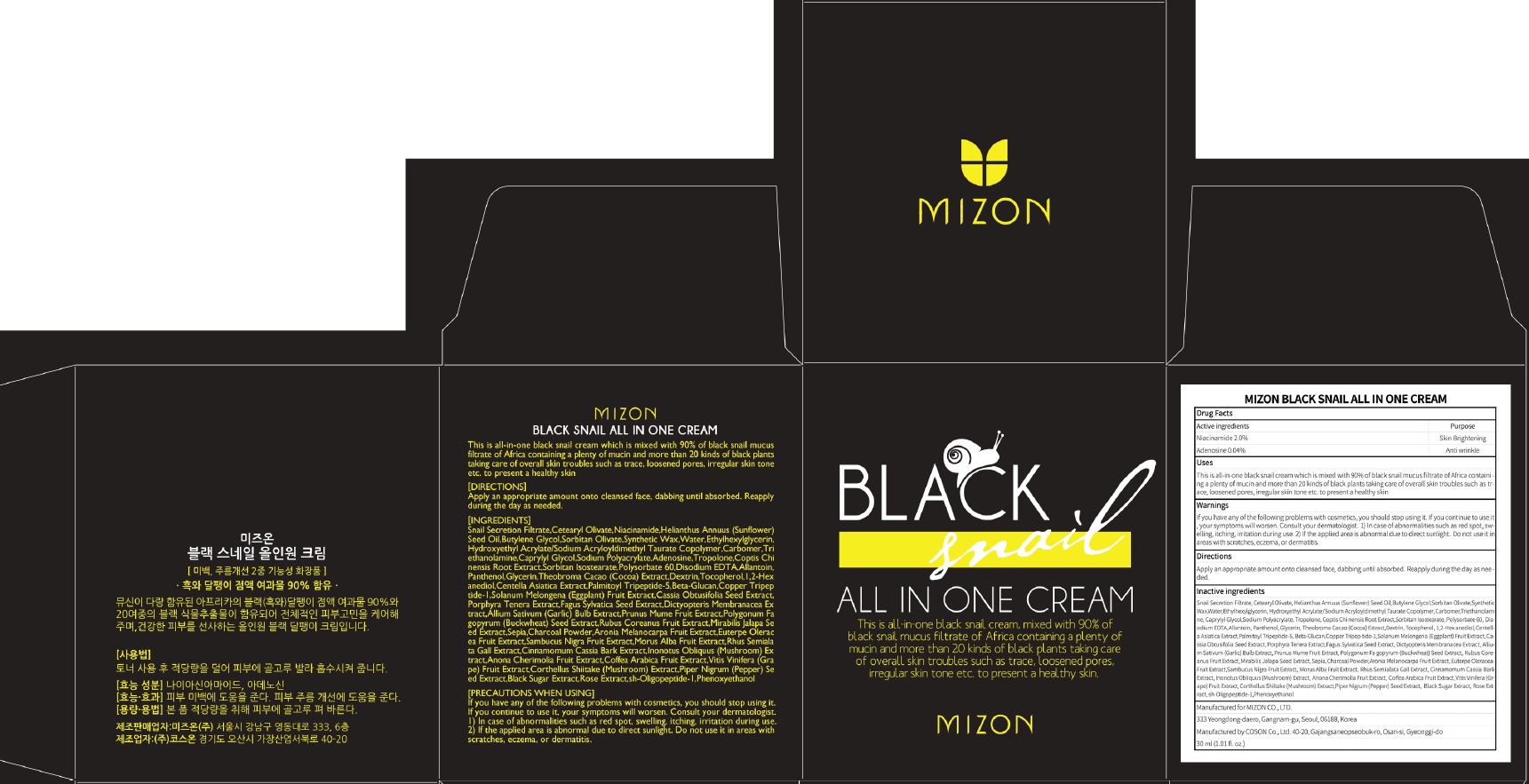 DRUG LABEL: MIZON BLACK SNAIL ALL IN ONE CREA M
NDC: 57718-310 | Form: CREAM
Manufacturer: MIZON CO.,LTD.
Category: otc | Type: HUMAN OTC DRUG LABEL
Date: 20180724

ACTIVE INGREDIENTS: Niacinamide 1.50 g/75 mL; Adenosine 0.03 g/75 mL
INACTIVE INGREDIENTS: Butylene Glycol; Sorbitan Olivate

ACTIVE INGREDIENT

Active ingredients: Niacinamide 2.0%, Adenosine 0.04%

INACTIVE INGREDIENT

Inactive ingredients:

Snail Secretion Filtrate,Cetearyl Olivate,Helianthus Annuus (Sunflower) Seed Oil,Butylene Glycol,Sorbitan Olivate,Synthetic Wax,Water,Ethylhexylglycerin, Hydroxyethyl Acrylate/Sodium Acryloyldimethyl Taurate Copolymer,Carbomer,Tri ethanolamine,Caprylyl Glycol,Sodium Polyacrylate, Tropolone,Coptis Chi nensis Root Extract,Sorbitan Isostearate,Polysorbate 60,Disodium EDTA,Allantoin, Panthenol,Glycerin,Theobroma Cacao (Cocoa) Extract,Dextrin,Tocopherol,1,2-Hex anediol,Centella Asiatica Extract,Palmitoyl Tripeptide-5,Beta-Glucan,Copper Tripep tide-1,Solanum Melongena (Eggplant) Fruit Extract,Cassia Obtusifolia Seed Extract, Porphyra Tenera Extract,Fagus Sylvatica Seed Extract,Dictyopteris Membranacea Ex tract,Allium Sativum (Garlic) Bulb Extract,Prunus Mume Fruit Extract,Polygonum Fa gopyrum (Buckwheat) Seed Extract,Rubus Coreanus Fruit Extract,Mirabilis Jalapa Se ed Extract,Sepia,Charcoal Powder,Aronia Melanocarpa Fruit Extract,Euterpe Olerac ea Fruit Extract,Sambucus Nigra Fruit Extract,Morus Alba Fruit Extract,Rhus Semiala ta Gall Extract,Cinnamomum Cassia Bark Extract,Inonotus Obliquus (Mushroom) Ex tract,Anona Cherimolia Fruit Extract,Coffea Arabica Fruit Extract,Vitis Vinifera (Gra pe) Fruit Extract,Corthellus Shiitake (Mushroom) Extract,Piper Nigrum (Pepper) Se ed Extract,Black Sugar Extract,Rose Extract,sh-Oligopeptide-1,Phenoxyethanol

PURPOSE

Purpose: Skin Brightening, Anti wrinkle

WARNINGS

If you have any of the following problems with cosmetics, you should stop using it. If you continue to use it, your symptoms will worsen. Consult your dermatologist. 1) In case of abnormalities such as red spot, swelling, itching, irritation during use. 2) If the applied area is abnormal due to direct sunlight. Do not use it in areas with scratches, eczema, or dermatitis.

KEEP OUT OF REACH OF CHILDREN

Uses

This is all-in-one black snail cream which is mixed with 90% of black snail mucus filtrate of Africa containing a plenty of mucin and more than 20 kinds of black plants taking care of overall skin troubles such as trace, loosened pores, irregular skin tone etc. to present a healthy skin

Directions

Apply an appropriate amount onto cleansed face, dabbing until absorbed. Reapply during the day as needed.